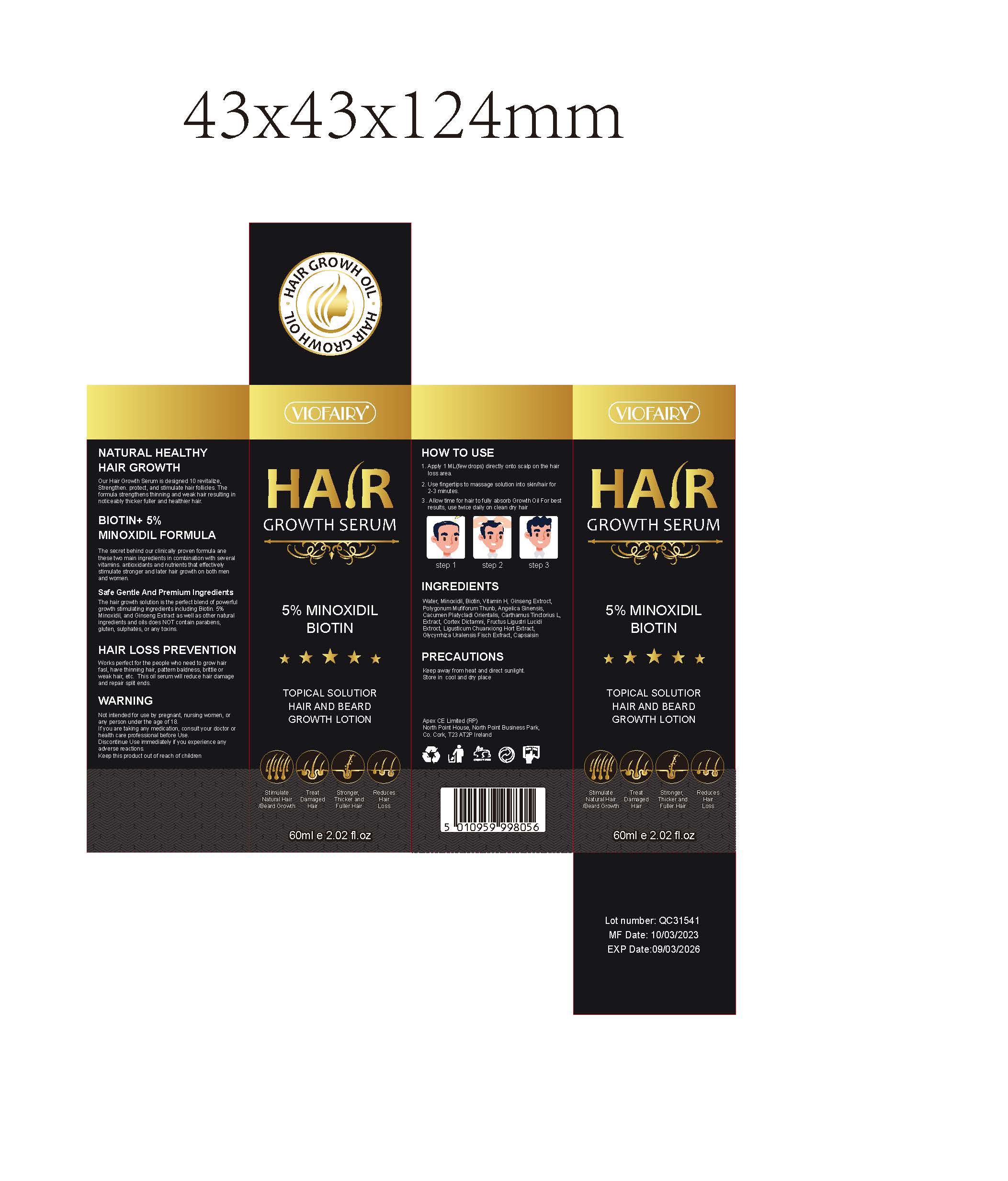 DRUG LABEL: Hair Serum
NDC: 83804-101 | Form: OIL
Manufacturer: Shenzhen Shandian Jingling Technology Co., Ltd.
Category: otc | Type: HUMAN OTC DRUG LABEL
Date: 20231211

ACTIVE INGREDIENTS: MINOXIDIL 0.05 g/1 mL
INACTIVE INGREDIENTS: WATER; ASIAN GINSENG; ANGELICA SINENSIS ROOT OIL; PLATYCLADUS ORIENTALIS LEAF; LIGUSTICUM SINENSE SUBSP. CHUANXIONG ROOT; CORDIA DICHOTOMA WHOLE; POLYGONATUM MULTIFLORUM ROOT; SAFFLOWER; BIOTIN

Hair Serum

Hair Serum

ACTIVE INGREDIENT

Minoxidil 5%

PURPOSE

HAIR LOSS PREVENTION
Works perfect for the people who need to grow hairfasl, have thinning hair, pattern baldness, brittle orweak hair etc. This oil serum will reduce hair damageand repair split ends.

INDICATIONS AND USAGE

Stimulate Natural Hair Beard Growth
Treat Damaged Hair
Stronger Thicker and Fuller Hair
Reduces Hair Loss

WARNINGS

Not intended for use by pregnant, nursing women, orany person under the age of 18.lfyou are taking any medication, consult your doctor orhealth care professional before UseDiscontinue Use immediately if you experience anyadverse reactions
Keep this product out of reach of children

DO NOT USE

Not intended for use by pregnant, nursing women, orany person under the age of 18.
lfyou are taking any medication, consult your doctor or
health care professional before Use

WHEN USING

1. Apply 1 ML(few drops) directly onto scalp on the hairloss area
2. Use fingertips to massage solution into skin!hair for2-3 minutes
3 .Allow time for hair tofully absorb Growth Oil For bestresults, use twice daily on clean dry hair

Discontinue Use immediately if you experience any
adverse reactions

Keep this product out of reach of children

DOSAGE AND ADMINISTRATION

1. Apply 1 ML(few drops) directly onto scalp on the hairloss area.
2. Use fingertips to massage solution into skinjhair for2-3 minutes.
3. Allow time for hair tofully absorb Growth Oil For bestresults, use twice daily on clean dry hair

STORAGE AND HANDLING

keep away from heat and direct sunlightStore in cool and dry place

INACTIVE INGREDIENT

Biotin
Water
Ginseng Extroct
polygonum multiflorum Thunb
Angelica Sinensis
Cacumen Platycladi Orientalis
Carthamus Tinctorius L Extract
Ligusticum Chuanxiong Hort Extract
Cortex Dictamni